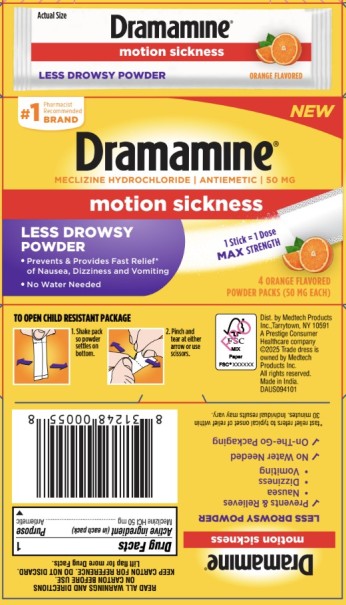 DRUG LABEL: DRAMAMINE
NDC: 63029-912 | Form: POWDER
Manufacturer: Medtech Products Inc.
Category: otc | Type: HUMAN OTC DRUG LABEL
Date: 20251218

ACTIVE INGREDIENTS: MECLIZINE DIHYDROCHLORIDE 50 mg/1 1
INACTIVE INGREDIENTS: ANHYDROUS CITRIC ACID; ASCORBIC ACID; ASPARTAME; BUTYLATED HYDROXYTOLUENE; STARCH, CORN; GUAR GUM; MALTODEXTRIN; MANNITOL; MICROCRYSTALLINE CELLULOSE; SILICON DIOXIDE; SORBITOL

Dramamine Less Drowsy Powder Orange

Drug Facts

Active ingredient (in each pack)

Meclizine HCl 50 mg

Purpose

Antiemetic

Use

For prevention and treatment of these symptoms associated with motion sickness:

■nausea ■vomiting ■dizziness

Warnings

Do not give to

children under 12 years of age unless directed by a doctor.

Ask a doctor before use if you have

■a breathing problem such as emphysema or chronic bronchitis

■glaucoma

■trouble urinating due to an enlarged prostate gland

Ask a doctor or pharmacist before use if you are taking

sedatives or tranquilizers.

When using this product

■drowsiness may occur

■avoid alcoholic drinks

■alcohol, sedatives, and tranquilizers may increase drowsiness

■be careful when driving a motor vehicle or operating machinery

If pregnant or breast-feeding,

ask a doctor before use.

Keep out of reach of children.

In case of overdose, get medical help or contact a Poison Control Center (1-800-222-1222) right away.

Directions

■take dose ½ to 1 hour before starting activity

■adults and children 12 years and over: place 1 packet on tongue once daily, or as directed by a doctor

Other information

■PHENYLKETONURICS: contains phenylalanine 1.68 mg per packet.

■store at room temperature 20°–25°C (68°-77°F)

Inactive ingredients

anhydrous citric acid, ascorbic acid, aspartame, butylated hydroxytoluene, corn starch, guar gum, maltodextrin, mannitol, microcrystalline cellulose, natural orange flavor, natural pink lemonade flavor, silicon dioxide, sorbitol.

Questions?

1-800-382-7219

Dramamine.com

PRINCIPAL DISPLAY PANEL

Dramamine®

Meclizine Hydrochloride | Antiemetic | 50 mg

Motion Sickness

Less Drowsy Powder

4 Orange Flavored Powder Packs (50 MG EACH)